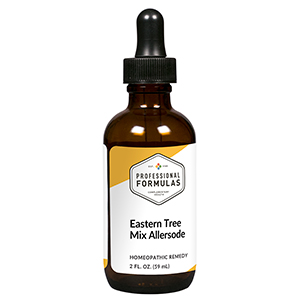 DRUG LABEL: Eastern Trees
NDC: 63083-1026 | Form: LIQUID
Manufacturer: Professional Complementary Health Formulas
Category: homeopathic | Type: HUMAN OTC DRUG LABEL
Date: 20190815

ACTIVE INGREDIENTS: FRAXINUS LATIFOLIA WHOLE 6 [hp_X]/59 mL; MILLETTIA PINNATA WHOLE 6 [hp_X]/59 mL; BETULA OCCIDENTALIS POLLEN 6 [hp_X]/59 mL; ELM 6 [hp_X]/59 mL; CARYA LACINIOSA BARK 6 [hp_X]/59 mL; ACER PENSYLVANICUM WHOLE 6 [hp_X]/59 mL; QUERCUS KELLOGGII POLLEN 6 [hp_X]/59 mL; LIRIODENDRON TULIPIFERA WHOLE 6 [hp_X]/59 mL; LIQUIDAMBAR STYRACIFLUA RESIN 6 [hp_X]/59 mL; SYMPHORICARPOS ALBUS FRUIT 6 [hp_X]/59 mL
INACTIVE INGREDIENTS: ALCOHOL; WATER

AEAST

ACTIVE INGREDIENTS

all the following at 6X, 12X, 30X:
Ash
Beech
Birch
Elm
Hickory
Maple
Oak
Poplar
Sweet gum
Sycamore

QUESTIONS

Professional Formulas

PO Box 2034 Lake Oswego, OR 97035

INDICATIONS

For the temporary relief of runny nose, sneezing, itching of the nose or throat, and itchy, watery eyes due to sensitivity to common tree allergens of the eastern United States.*

PURPOSE

*Claims based on traditional homeopathic practice, not accepted medical evidence. Not FDA evaluated.

WARNINGS

In case of overdose, get medical help or contact a poison control center right away.

Keep out of the reach of children.

PREGNANCY OR BREAST FEEDING

If pregnant or breastfeeding, ask a healthcare professional before use.

DIRECTIONS

Place drops under tongue 30 minutes before/after meals. Adults and children 12 years and over: Take 10 to 15 drops up to 3 times per day. For desensitization, begin with 1 to 5 drops daily, increasing to the standard dose gradually to avoid symptom expression; after 1 to 3 months at the standard dose, decrease gradually to a maintenance dose of 10 to 15 drops weekly. Consult a physician for use in children under 12 years of age.

OTHER INFORMATION

Tamper resistant. If seal is broken, do not use. After opening, close container tightly and store at room temperature away from heat.

INACTIVE INGREDIENTS

20% ethanol, purified water.

LABEL

Est 1985

Professional Formulas

Complementary Health

Eastern Trees

Homeopathic Remedy

2 FL. OZ. (59 mL)